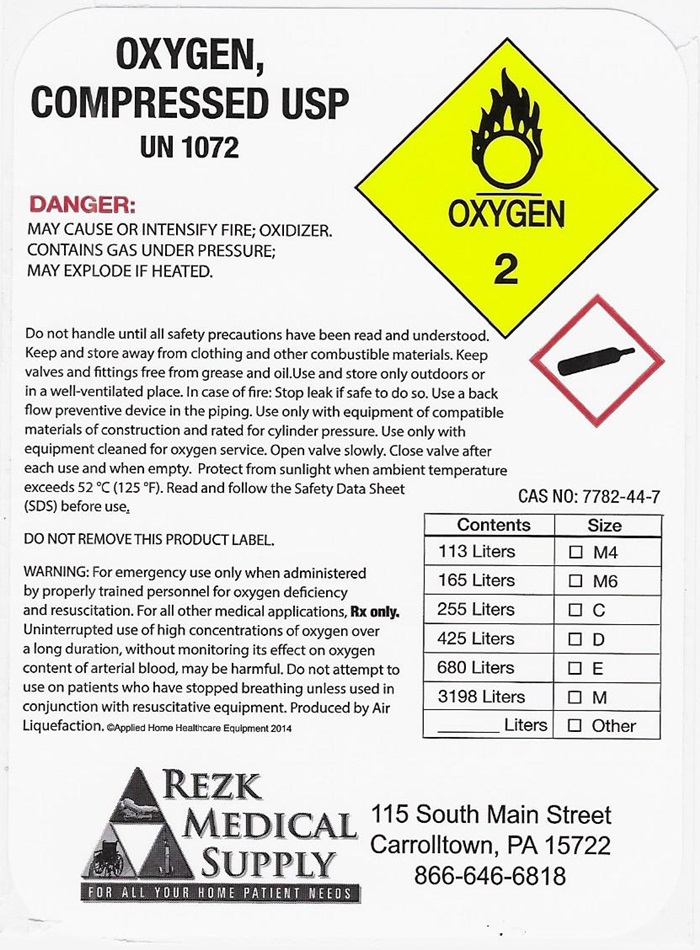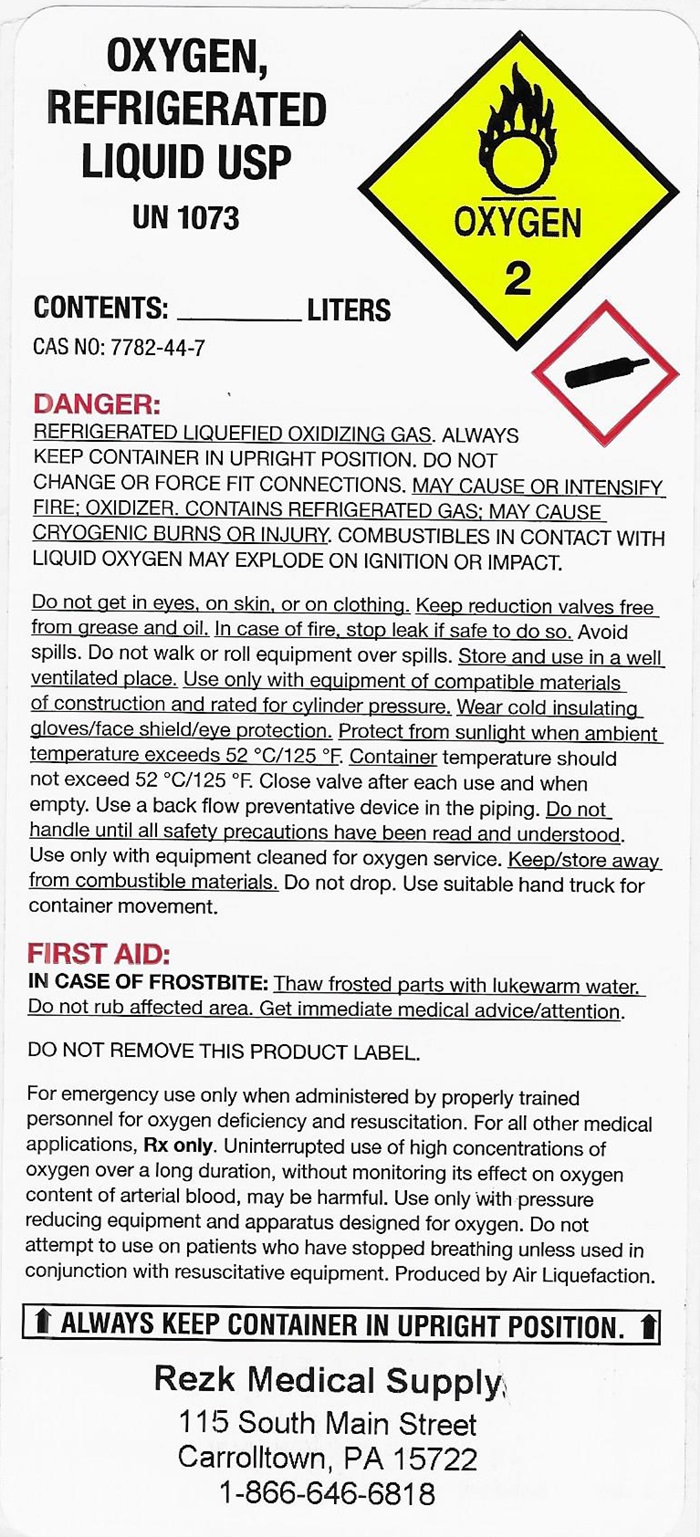 DRUG LABEL: OXYGEN
NDC: 52751-001 | Form: GAS
Manufacturer: Rezk Medical Supply
Category: prescription | Type: HUMAN PRESCRIPTION DRUG LABEL
Date: 20191028

ACTIVE INGREDIENTS: OXYGEN 99 L/100 L

Oxygen

OXYGEN COMPRESSED LABEL

OXYGEN, COMPRESSED USP UN1072 OXYGEN 2

DANGER: MAY CAUSE OR INTENSIGY FIRE; OXIDIZER. CONTAINS GAS UNDER PRESSURE; MAY EXPLODE IF HEATED.

Do not handle until all safety precautions have been read and understood. Keep and store away from clothing and other combustible materials. Keep valves and fittings from grease and oil. Use and store only outdoors or in a well-ventilated place. Incase of fire: Stop leak if safe to do so. Use a back flow preventive device in the piping. Use only with equipment of compatible materials of construction and rated for cylinder pressure. Use only with equipment cleaned for oxygen service. Open valve slowly. Close valve after each use and when empty. Protect from sunlight and ambient temperature exceeds 52°C (125°F). Read and follow the Safety Data Sheet (SDS) before use.

DO NOT REMOVE THIS PRODUCT LABEL.

WARNING: For emergency use only when administered by properly trained personnel for oxygen deficiency and resuscitation. For all other medical applications, Rx only. Uninterrupted use of high concentrations of oxygen over a long duration, without monitoring its effect on oxygen content of arterial blood, may be harmful. Do not attempt to use on patients who have stopped breathing unless used in conjunction with resuscitative equipment. Produced by Air Liquefaction. ©Applied Home Healthcare Equipment 2014

CAS NO: 7782-44-7

Contents Size

113 Liters __M4

165 Liters __M6

255 Liters __ C

425 Liters __ D

680 Liters __ E

7080 Liters __ H

___ Liters __ Other

REZK MEDICAL SUPPLY

FOR ALL YOUR HOME PATIENT NEEDS

115 South Main Street

Carrolltown, PA 15722

866-646-6818

OXYGEN, REFRIGERATED LIQUID USP UN 1073 OXYGEN 2

CONTENTS: ______________LITERS

CAS NO: 7782-44-7

DANGER: REFRIGERATED LIQUEFIED OXIDIZING GAS. ALWAYS KEEP CONTAINER IN UPRIGHT POSITION. DO NOT CHANGE OR FORCE FIT CONNECTIONS. MAY CAUSE OR INTENSIFY FIRE; OXIDIZER, CONTAINS REFRIGERATED GAS; MAY CAUSE CRYOGENIC BURNS OR INJURY. COMBUSTIBLES IN CONTACT WITH LIQUID OXYGEN MAY EXPLODE ON IGNITION OR IMPACT.

Do not get in eyes, on skin, or on clothing. Keep reduction valves free from grease and oil. In case of fire, stop leak if safe to do so. Avoid spills. Do not walk or roll equipment over spills. Store and use in a well ventilated place. Use only with equipment of compatible materials of construction and rated for cylinder pressure. Wear cold insulating gloves/face shield/eye protection. Protect from sunlight when ambient temperature exceeds 52°C/125°F. Container temperature should not exceed 52°C/125°F. Close valve after each use and when empty. Use a back flow preventative device in the piping. Do not handle until all safety precautions have been read and understood. Use only with equipment cleaned for oxygen service. Keep/store away from combustible materials. Do not drop. Use suitable hand truck for container movement.

FIRST AID:

IN CASE OF FROSTBITE: Thaw frosted parts with lukewarm water. Do not rub affected area. Get immediate medical advice/attention.

DO NOT REMOVE THIS PRODUCT LABEL

For emergency use only when administered by properly trained personnel for oxygen deficiency and resuscitation. For all other medical applications, Rx only. Uninterrupted use of high concentrations of oxygen over a long duration, without monitoring its effect on oxygen content of arterial blood, may be harmful. Use only with pressure reducing equipment and apparatus designed for oxygen. Do not attempt to use on patients who have stopped breathing unless used in conjunction with resuscitative equipment. Produced by Air Liquefaction.

!ALWAYS KEEP CONTAINER IN UPRIGHT POSITION!

Rezk Medical Supply

115 South Main Street

Carrolltown, PA 15722

1-866-646-6818